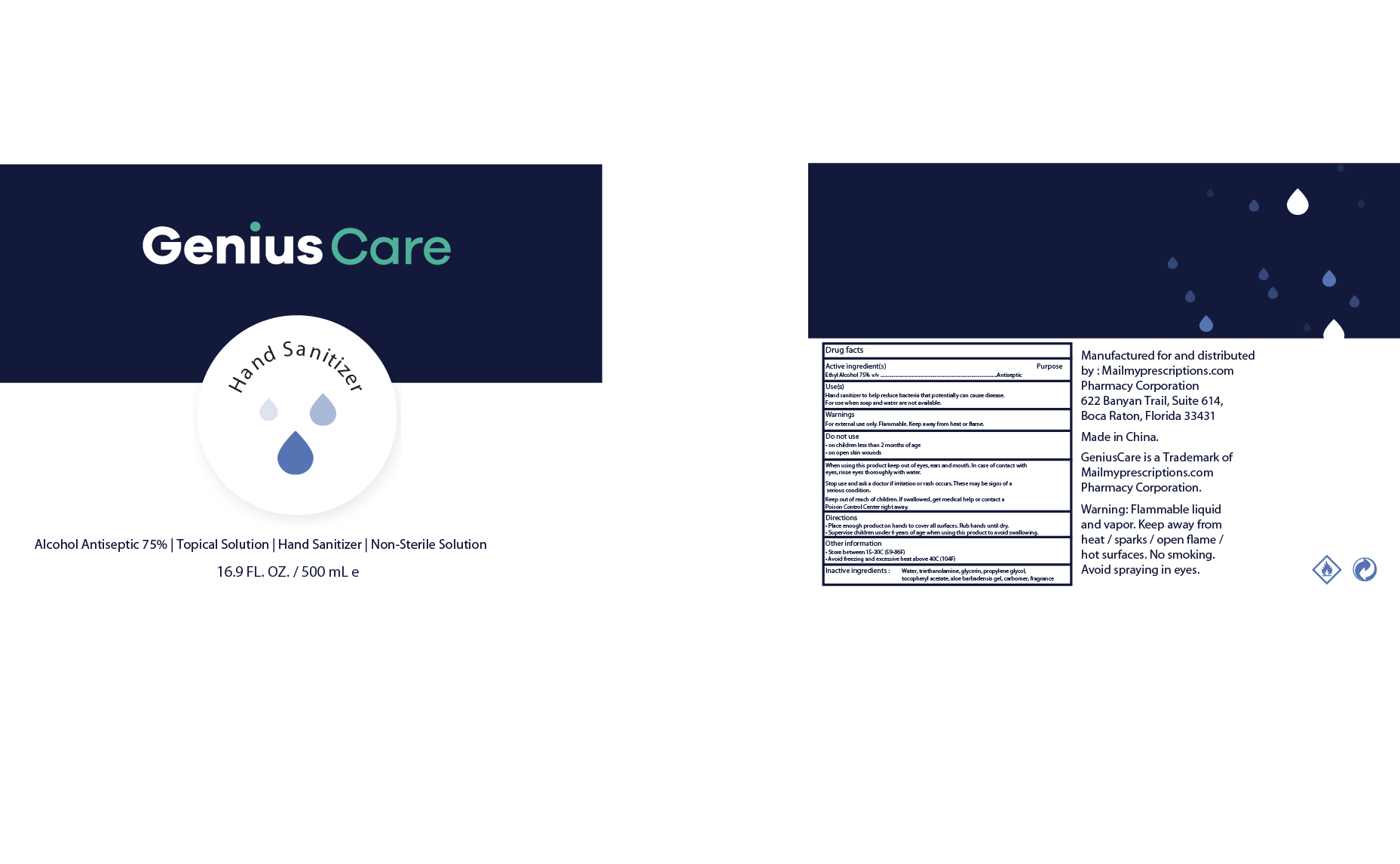 DRUG LABEL: Genius Care Hand Sanitizer 75 Percent Alcohol
NDC: 76114-008 | Form: SOLUTION
Manufacturer: Zhejiang Aidi Cosmetics Co., Ltd
Category: otc | Type: HUMAN OTC DRUG LABEL
Date: 20200512

ACTIVE INGREDIENTS: ALCOHOL 75 mL/100 mL
INACTIVE INGREDIENTS: GLYCERIN; WATER; CARBOMER 934; PROPYLENE GLYCOL; ALPHA-TOCOPHEROL ACETATE; TROLAMINE; ALOE VERA WHOLE

NA

Active Ingredient(s)

Ethyl Alcohol 75% v/v

Purpose

Antispetic

Use

Hand sanitizer to help reduce bacteria that potentially can cause disease

For use when soap and water are not available

Warnings

For external use only

Flammable. Keep away from heat or flame

Do not use

- on children less tha two months of age
- on open skin wounds

When using this product keep out of eyes, ears, and mouth. In case of contact with eyes, rinse eyes thoroughly with water.

Stop use and ask a doctor if irritation or rash occurs. These may be signs of serious condition

Keep out of reach of children. If swallowed, get medical help or contact a Poison Control Center right away.

Directions

Place enough product on hands to cover all surfaces. Rub hands untill dry

Supervise children under six years of age when using this product to avoid swallowing

Other information

Store between 15-30 C (59 to 86F)

Avoid freezing and excessive heat above 40C (104F)

Inactive ingredients

Water, triethanolamine, glycerin, propylene glycol, tocopheryl acetate, aloe barbadensis gel, carbomer, fragrance